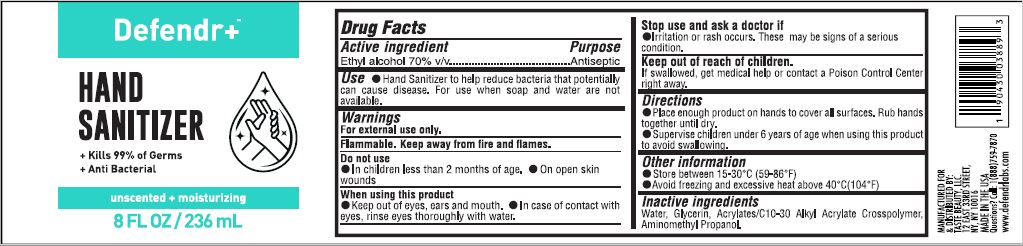 DRUG LABEL: DEFENDR Hand Sanitizer
NDC: 74825-5071 | Form: GEL
Manufacturer: TASTE BEAUTY LLC
Category: otc | Type: HUMAN OTC DRUG LABEL
Date: 20201009

ACTIVE INGREDIENTS: ALCOHOL 70 mL/100 mL
INACTIVE INGREDIENTS: AMINOMETHYLPROPANOL 0.75 mL/100 mL; GLYCERIN 0.1 mL/100 mL; CARBOMER 940 0.5 mL/100 mL; WATER 33.3 mL/100 mL

DEFENDR+ Hand Sanitizer

Defendr Hand Sanitizer is a a human over the counter drug product labeled by Taste Beauty Llc. The generic name of Defendr Hand Sanitizer is alcohol. The product's dosage form is gel and is administered via topical form.

Active Ingredient(s)

Ethyl Alcohol 70% v/v. Purpose: Antiseptic

Purpose

Antiseptic, Hand Sanitizer

Use

Hand Sanitizer to help reduce bacteria that potentially can cause disease. For use when soap and water are not available.

Warnings

For external use only. Flammable. Keep away from heat or flame

Do not use

- in children less than 2 months of age
- on open skin wounds

When using this product keep out of eyes, ears, and mouth. In case of contact with eyes, rinse eyes thoroughly with water.
Stop use and ask a doctor if irritation or rash occurs. These may be signs of a serious condition.
Keep out of reach of children. If swallowed, get medical help or contact a Poison Control Center right away.

Stop use and ask a doctor if irritation or rash occurs. These may be signs of a serious condition.

Keep out of reach of children. If swallowed, get medical help or contact a Poison Control Center right away.

Directions

- Place enough product on hands to cover all surfaces. Rub hands together until dry.
- Supervise children under 6 years of age when using this product to avoid swallowing.

Other information

- Store between 15-30C (59-86F)
- Avoid freezing and excessive heat above 40C (104F)

Inactive ingredients

Deionized water, Acrylates/C10-30 alkyl acrylate crosspolymer, Triethanolamine, EDTA.